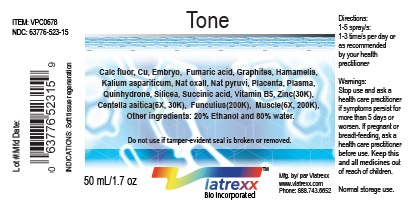 DRUG LABEL: Viatrexx-Tone
NDC: 63776-523 | Form: SPRAY
Manufacturer: VIATREXX BIO INCORPORATED
Category: homeopathic | Type: HUMAN OTC DRUG LABEL
Date: 20190319

ACTIVE INGREDIENTS: Calcium Fluoride 30 [kp_C]/1 mL; Centella Asiatica 30 [kp_C]/1 mL; Copper 30 [kp_C]/1 mL; Sus Scrofa Embryo 30 [kp_C]/1 mL; Human Embryo Tissue 30 [kp_C]/1 mL; Fumaric Acid 30 [kp_C]/1 mL; Bos Taurus Umbilical Cord 200 [kp_C]/1 mL; Sus Scrofa Umbilical Cord 200 [kp_C]/1 mL; Graphite 30 [kp_C]/1 mL; Witch Hazel 30 [kp_C]/1 mL; Potassium Aspartate 30 [kp_C]/1 mL; Pork 200 [kp_C]/1 mL; Beef 200 [kp_C]/1 mL; Sodium Diethyl Oxalacetate 30 [kp_C]/1 mL; Sodium Pyruvate 30 [kp_C]/1 mL; Bos Taurus Placenta 30 [kp_C]/1 mL; Sus Scrofa Placenta 30 [kp_C]/1 mL; Human Placental Tissue 30 [kp_C]/1 mL; Human Plasma 30 [kp_C]/1 mL; Quinhydrone 30 [kp_C]/1 mL; Silicon Dioxide 30 [kp_C]/1 mL; Succinic Acid 30 [kp_C]/1 mL; Pantothenic Acid 30 [kp_C]/1 mL; Zinc 30 [kp_C]/1 mL
INACTIVE INGREDIENTS: Alcohol; Water

Tone

Active Ingredients

Calcarea fluorica (30K), Centella asiatica (6X, 30K), Cu (30K), Embryo (30K), Fumaric acid (30K), Funiculus (200K), Graphites (30K), Hamamelis (30K), Kalium aspariticum (30K), Muscle (6X, 200K), Natrum oxalaceticum (30K), Natrum pyruvicum (30K), Placenta (30K), Plasma (30K), Quinhydrone (30K), Silicea (30K), Succinic acid (30K), Vitamin B5 (30K), Zinc (30K).

Purpose

Calcarea fluorica
Centella asiatica
Cu
Embryo
Fumaric acid
Funiculus
Graphites
Hamamelis
Kalium aspariticum
Muscle
Natrum oxalaceticum
Natrum pyruvicum
Placenta
Plasma
Quinhydrone
Silicea
Succinic acid
Vitamin B5
Zinc

Drainage
Adaptogen
Metabolism
Regeneration
Cell respiration
Regeneration
Drainage
Venous support
Cell respiration
Regeneration
Cell respiration
Cell respiration
Regeneration
Regeneration
Metabolism
Drainage
Cell respiration
Metabolism
Neurological support

Description

Viatrexx-Tone is a homeopathic product composed of physiological (low dose and low low dose) natural micro nutrients. These nano particles are designed to nourish the system.

Uses

Soft tissue regeneration.

Warnings

Stop use and ask a health care practitioner if symptoms persist for more than 5 days or worsen. If pregnant or breastfeeding, ask a health care practitioner before use.

Dosage

1-3 spray(s); 1-3 time(s) per day or as recommended by your health care practitioner.

Inactive Ingredients

Alcohol 20% and Water 80%

Product availability

Product may be acquired in 0.5, 30 ,50, 100, 250, 500 and 1,000 mL bottles.

References upon request

To report SUSPECTED ADVERSE REACTIONS, contact the FDA at 1-800-FDA-1088 or www.fda.gov/medwatch

Distributed by
Viatrexx Bio Incorporated
Newark, DE, USA, 19713

Manufactured by
8046255 Canada Inc
Beloeil, Qc, J3G 6S3
Date of last revision March 2019

For Questions and comments
Info@Viatrexx.com
www.Viatrexx.com

PACKAGE LABEL.PRINCIPAL DISPLAY PANEL

NDC: 63776-523-11
Item: VPC0678
Viatrexx Bio Incorporated
Viatrexx-Tone
0.5 mL ampule
For Oral and Topical Use
Expiry date: Lot #:
Manufactured for:
Viatrexx Bio Incorporated Newark, DE, USA, 19713
www.Viatrexx.com
Ingredients, homeopathic
See insert or www.viatrexx.com
Inactives: Alcohol 20%, Water 80%

NDC: 63776-523-14
Item: VPC0678
Viatrexx Bio Incorporated
Viatrexx-Tone
Box of 1 X 30 mL spray bottle
For Oral and Topical Use
Expiry date: Lot #:
Manufactured for:
Viatrexx Bio Incorporated Newark, DE, USA, 19713
www.Viatrexx.com
Ingredients, homeopathic
See insert or www.viatrexx.com
Inactives: Alcohol 20%, Water 80%

NDC: 63776-523-15
Item: VPC0678
Viatrexx Bio Incorporated
Viatrexx-Tone
50 mL spray bottle
For Oral and Topical Use
Expiry date: Lot #:
Manufactured for:
Viatrexx Bio Incorporated Newark, DE, USA, 19713
www.Viatrexx.com
Ingredients, homeopathic
See insert or www.viatrexx.com
Inactives: Alcohol 20%, Water 80%

NDC: 63776-523-16
Item: VPC0678
Viatrexx Bio Incorporated
Viatrexx-Tone
100 mL bottle
For Oral and Topical Use
Expiry date: Lot #:
Manufactured for:
Viatrexx Bio Incorporated Newark, DE, USA, 19713
www.Viatrexx.com
Ingredients, homeopathic
See insert or www.viatrexx.com
Inactives: Alcohol 20%, Water 80%

NDC: 63776-523-17
Item: VPC0678
Viatrexx Bio Incorporated
Viatrexx-Tone 250 mL spray bottle
For Oral and Topical Use
Expiry date: Lot #:
Manufactured for:
Viatrexx Bio Incorporated Newark, DE, USA, 19713
www.Viatrexx.com
Ingredients, homeopathic
See insert or www.viatrexx.com
Inactives: Alcohol 20%, Water 80%